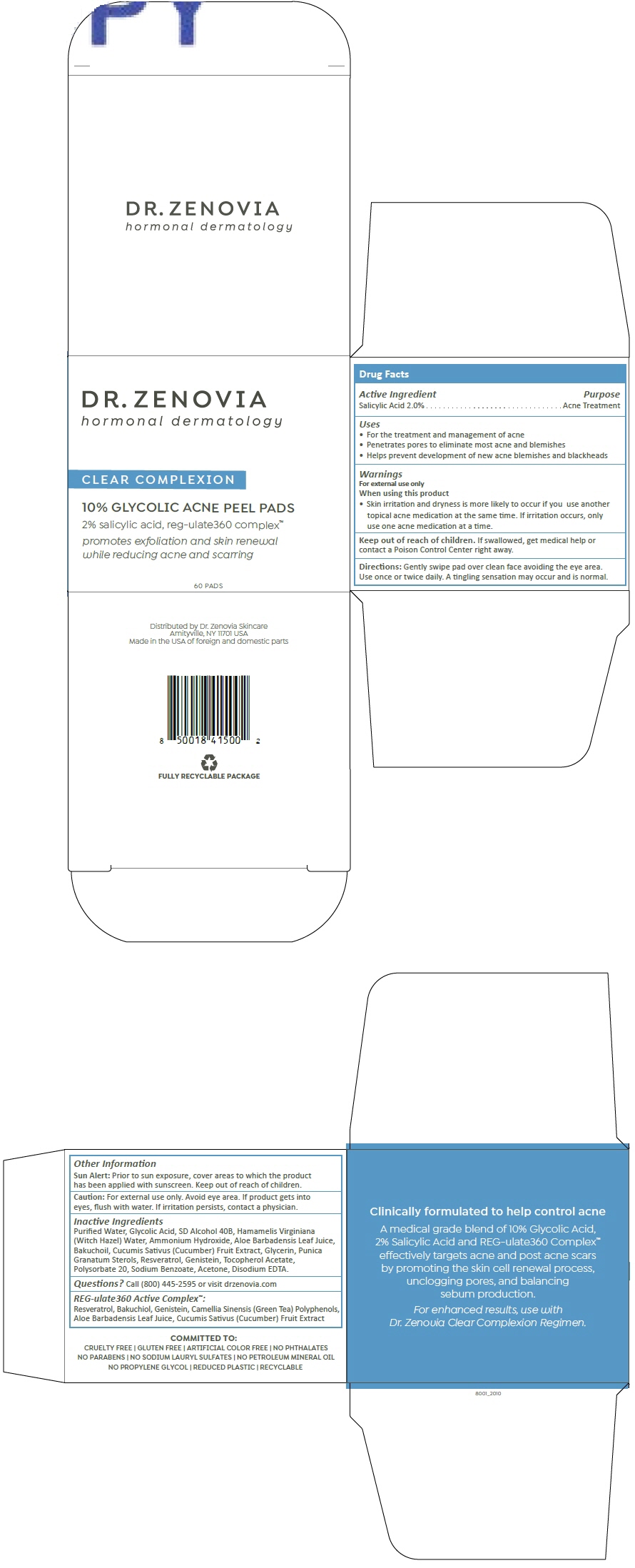 DRUG LABEL: Dr. Zenovia Clear Complexion
NDC: 51326-801 | Form: CLOTH
Manufacturer: Topiderm, Inc.
Category: otc | Type: HUMAN OTC DRUG LABEL
Date: 20240628

ACTIVE INGREDIENTS: SALICYLIC ACID 20 mg/1 1
INACTIVE INGREDIENTS: WATER; GLYCOLIC ACID; ALCOHOL; HAMAMELIS VIRGINIANA TOP WATER; AMMONIA; ALOE VERA LEAF; BAKUCHIOL; CUCUMBER; GLYCERIN; PUNICA GRANATUM STEROLS; RESVERATROL; GENISTEIN; .ALPHA.-TOCOPHEROL ACETATE; POLYSORBATE 20; SODIUM BENZOATE; ACETONE; EDETATE DISODIUM

Dr. Zenovia Clear Complexion

Drug Facts

Active Ingredient

Salicylic Acid 2.0%

Purpose

Acne Treatment

Uses

- For the treatment and management of acne
- Penetrates pores to eliminate most acne and blemishes
- Helps prevent development of new acne blemishes and blackheads

Warnings

For external use only

When using this product

- Skin irritation and dryness is more likely to occur if you use another topical acne medication at the same time. If irritation occurs, only use one acne medication at a time.

Keep out of reach of children. If swallowed, get medical help or contact a Poison Control Center right away.

Directions

Gently swipe pad over clean face avoiding the eye area. Use once or twice daily. A tingling sensation may occur and is normal.

Other Information

Sun Alert

Prior to sun exposure, cover areas to which the product has been applied with sunscreen. Keep out of reach of children.

Caution

For external use only. Avoid eye area. If product gets into eyes, flush with water. If irritation persists, contact a physician.

Inactive Ingredients

Purified Water, Glycolic Acid, SD Alcohol 40B, Hamamelis Virginiana (Witch Hazel) Water, Ammonium Hydroxide, Aloe Barbadensis Leaf Juice, Bakuchoil, Cucumis Sativus (Cucumber) Fruit Extract, Glycerin, Punica Granatum Sterols, Resveratrol, Genistein, Tocopherol Acetate, Polysorbate 20, Sodium Benzoate, Acetone, Disodium EDTA.

Questions?

Call (800) 445-2595 or visit drzenovia.com

REG-ulate360 Active Complex™

Resveratrol, Bakuchiol, Genistein, Camellia Sinensis (Green Tea) Polyphenols, Aloe Barbadensis Leaf Juice, Cucumis Sativus (Cucumber) Fruit Extract

Distributed by Dr. Zenovia Skincare
Amityville, NY 11701 USA

PRINCIPAL DISPLAY PANEL - 60 Pad Bottle Box

DR. ZENOVIA
hormonal dermatology

CLEAR COMPLEXION

10% GLYCOLIC ACNE PEEL PADS

2% salicylic acid, reg-ulate360 complex™

promotes exfoliation and skin renewal
while reducing acne and scarring

60 PADS